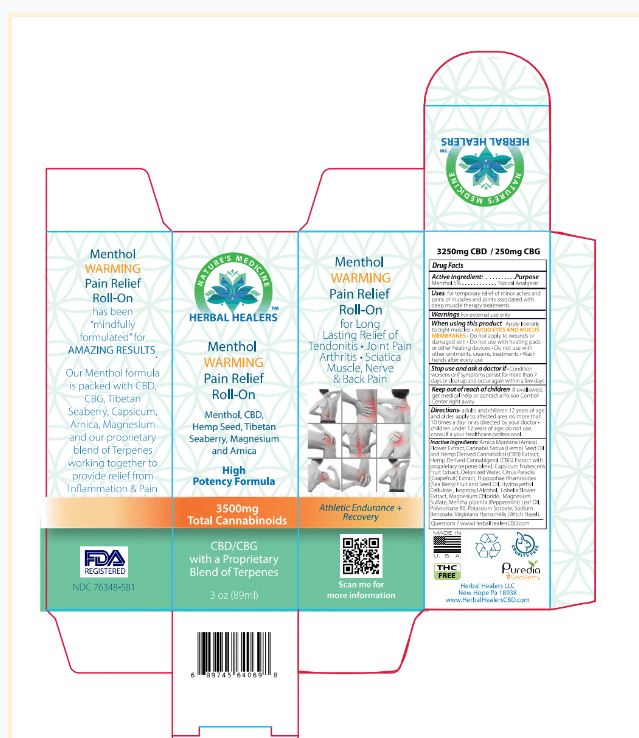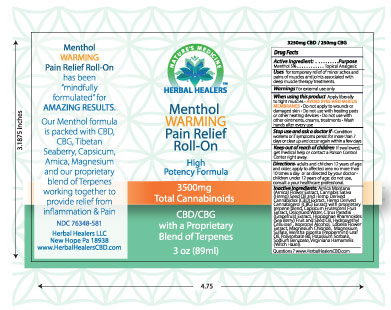 DRUG LABEL: Herbal Healers Menthol Warming Roll On
NDC: 76348-581 | Form: LIQUID
Manufacturer: Renu Laboratories, Inc.
Category: otc | Type: HUMAN OTC DRUG LABEL
Date: 20220114

ACTIVE INGREDIENTS: MENTHOL 4.2 g/84 g
INACTIVE INGREDIENTS: SODIUM BENZOATE; WATER; WITCH HAZEL; LOBELIA INFLATA; MAGNESIUM CHLORIDE; ARNICA MONTANA FLOWER; HIPPOPHAE RHAMNOIDES FRUIT OIL; ISOPROPYL ALCOHOL; CANNABIGEROL; LIMONENE, (+)-; POTASSIUM SORBATE; .ALPHA.-PINENE; LINALOOL, (+)-; HIPPOPHAE RHAMNOIDES SEED OIL; CANNABIDIOL; CANNABIS SATIVA SEED OIL; MAGNESIUM SULFATE, UNSPECIFIED; PEPPERMINT OIL; METHYLCELLULOSE (4000 CPS); TERPINOLENE; POLYSORBATE 80; CARYOPHYLLENE; MYRCENE

Herbal Healers Warming Menthol Pain Relief Roll-on

ACTIVE INGREDIENT

Menthol 5%

PURPOSE

Topical Analgesic

INDICATIONS AND USAGE

Uses for temporary relief of minor aches and pains of muscles and joints associated with deep muscle therapy treatments.

WARNINGS

For external use only

WHEN USING

Do not bandage tightly

- avoid contact with eyes
- do not apply to wounds or damaged skin
- do not use with heating pads or other heating devices.

Stop use and ask a doctor if

Condition worsens of if symptoms persist for more then 7 days or clear p and occur again within a few days

Keep out of reach of children

If swallowed, get medical help or contact a Poison Control Center right away.

Directions

adults and children 12 years of age and older, apply to affected area no more than 10 times a day or as directed by your doctor

children under 12 years of age, do not use. Consult a healthcare professional.

INACTIVE INGREDIENT

Arnica Montana (Arnica) Flower Extract, Cannabis Sativa (Hemp) Seed Oil and Hemp Derived Cannabidiol (CBD) Extract, Hemp Derived Cannabigerol (CBG) Extract with proprietary terpene blend (Alpha Pinene, Beta Caryophyllene, Myrcene, Limonene, Linalool, Terpinolene), Capsicum frutescens extract, Deionized Water, Citrus Paradisi (Grapefruit) Extract, Hippophae Rhamnoides (Sea Berry) Fruit and Seed Oil, Hydroxyethyl Celluose, Isopropyl Alcohol, Lobelia Flower Extract, Magnesium Chloride, Magnesium Sulfate, Mentha piperita (Peppermint) Leaf Oil, Polysorbate 80, Potassium Sorbate, Sodium Benzoate, Virginiana Hamamelis (Witch Hazel).

Questions ? www.HerbalHealersCBD.com

STATEMENT OF IDENTITY

HERBAL HEALERS

Menthol WARMING

Pain Relief

Roll-On

WARMING PAIN RELIEF ROLL-ON LABEL AND BOX

BOX ART